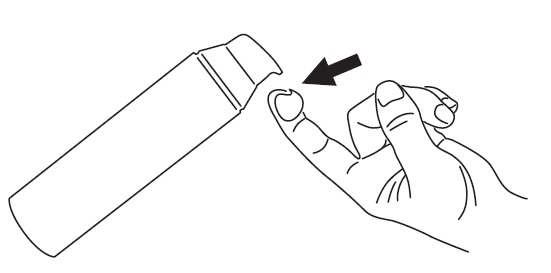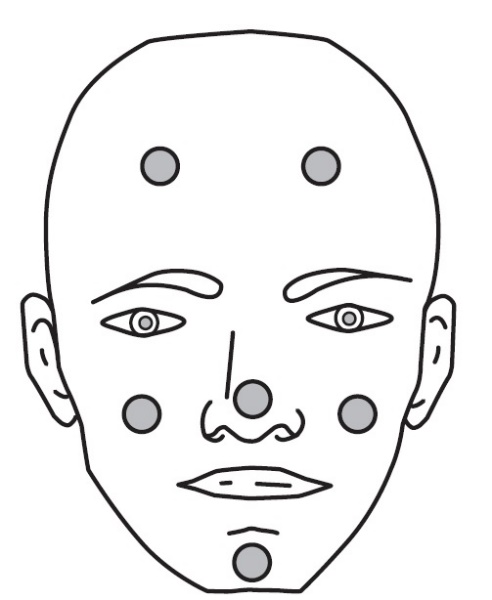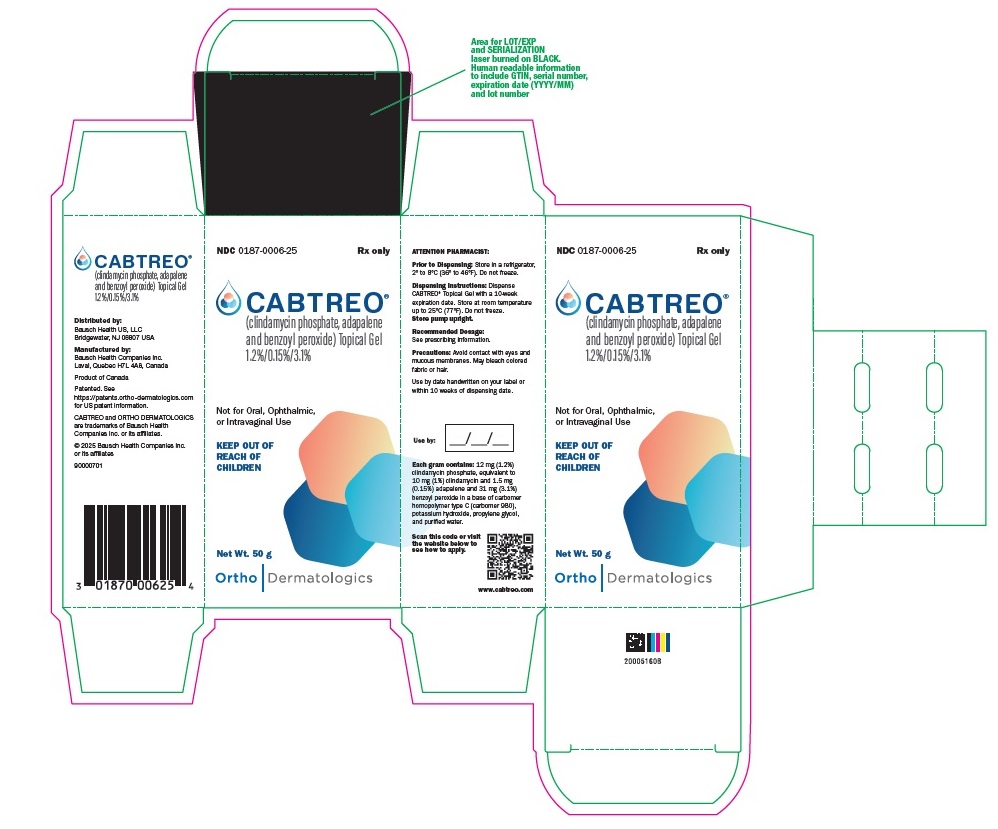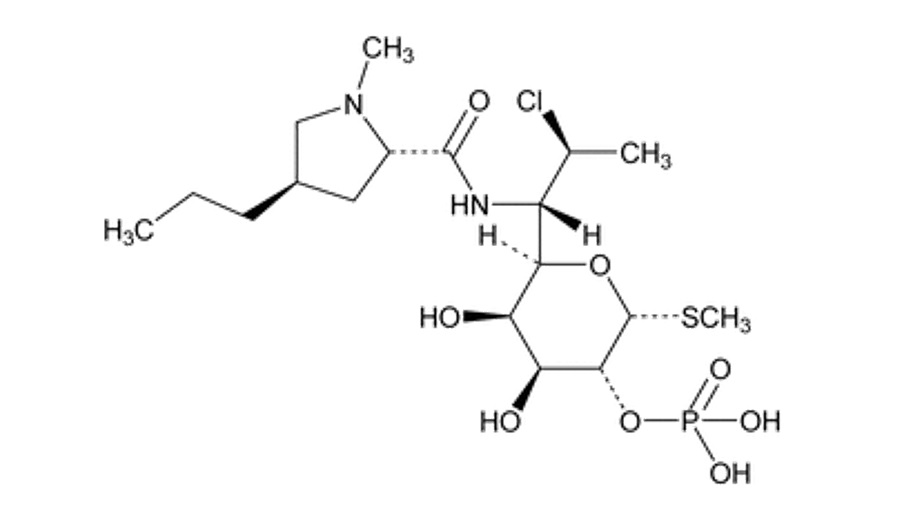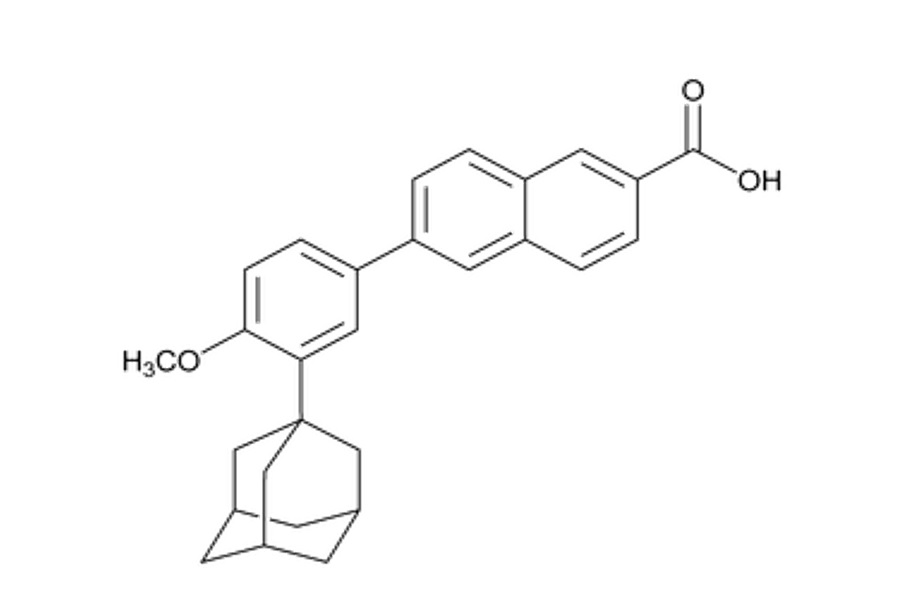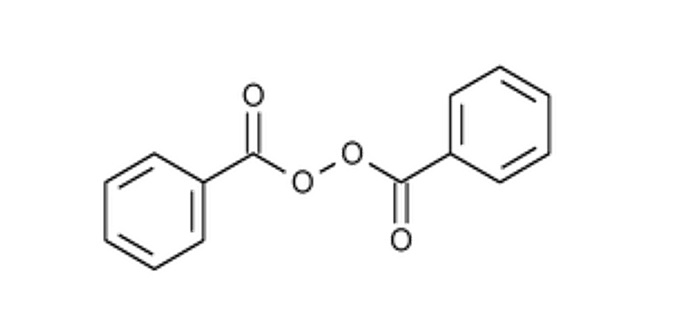 DRUG LABEL: Cabtreo
NDC: 0187-0006 | Form: GEL
Manufacturer: Bausch Health US LLC
Category: prescription | Type: HUMAN PRESCRIPTION DRUG LABEL
Date: 20250424

ACTIVE INGREDIENTS: CLINDAMYCIN PHOSPHATE 12 mg/1 g; BENZOYL PEROXIDE 31 mg/1 g; ADAPALENE 1.5 mg/1 g
INACTIVE INGREDIENTS: CARBOMER HOMOPOLYMER TYPE C (ALLYL PENTAERYTHRITOL CROSSLINKED); POTASSIUM HYDROXIDE; PROPYLENE GLYCOL; WATER

HIGHLIGHTS OF PRESCRIBING INFORMATION

These highlights do not include all the information needed to use CABTREO safely and effectively. See full prescribing information for CABTREO.
CABTREO®(clindamycin phosphate, adapalene, and benzoyl peroxide) topical gel
Initial U.S. Approval: 2023

1 INDICATIONS AND USAGE

CABTREO is a combination of clindamycin phosphate (a lincosamide antibacterial), adapalene (a retinoid), and benzoyl peroxide indicated for the topical treatment of acne vulgaris in adult and pediatric patients 12 years of age and older. (1)

2 DOSAGE AND ADMINISTRATION

- Apply a thin layer of CABTREO to the affected areas once daily. (2)
- Avoid the eyes, mouth, paranasal creases, mucous membranes, and areas of broken, eczematous, or sunburned skin. (2)
- Not for oral, ophthalmic, or intravaginal use. (2)

3 DOSAGE FORMS AND STRENGTHS

Topical gel: 1.2% clindamycin phosphate, 0.15% adapalene, and 3.1% benzoyl peroxide. CABTREO is supplied in 20-gram and 50-gram pumps. (3)

4 CONTRAINDICATIONS

- Known hypersensitivity to clindamycin, adapalene, benzoyl peroxide, any components of the formulation, or lincomycin. (4)
- History of regional enteritis, ulcerative colitis, or antibiotic-associated colitis. (4)

5 WARNINGS AND PRECAUTIONS

- Hypersensitivity: If a serious hypersensitivity reaction occurs, discontinue CABTREO immediately and initiate appropriate therapy. (5.1)
- Colitis: Clindamycin can cause severe colitis, which may result in death. Discontinue CABTREO if diarrhea occurs. (5.2)
- Photosensitivity: Avoid or minimize exposure to sunlight and sunlamps. Wear sunscreen and protective clothing when sun exposure cannot be avoided. (5.3)
- Skin Irritation and Allergic Contact Dermatitis: Erythema, scaling, dryness, stinging/burning, irritant and allergic contact dermatitis may occur with use of CABTREO and may necessitate discontinuation (5.4)

6 ADVERSE REACTIONS

The most common adverse reactions (occurring in >1% of the CABTREO group and greater than the vehicle group) were application site reactions, pain, erythema, dryness, irritation, exfoliation, and dermatitis. (6.1)

To report SUSPECTED ADVERSE REACTIONS, contact Bausch Health US, LLC at 1-800-321-4576 or FDA at 1-800-FDA-1088 or www.fda.gov/medwatch.

7 DRUG INTERACTIONS

- Neuromuscular Blocking Agents:Use CABTREO with caution in patients receiving neuromuscular blocking agents. (7)

FULL PRESCRIBING INFORMATION

1 INDICATIONS AND USAGE

CABTREO is indicated for the topical treatment of acne vulgaris in adult and pediatric patients 12 years of age and older.

2 DOSAGE AND ADMINISTRATION

Cleanse the affected area gently. After the skin is dry, apply a thin layer of CABTREO to the affected area once daily.

Wash hands thoroughly after application of CABTREO.

Avoid the eyes, mouth, paranasal creases, mucous membranes, and areas of broken, eczematous, or sunburned skin [ see Warnings and Precautions (5.3)].

CABTREO is for topical use only. Not for oral, ophthalmic, or intravaginal use.

3 DOSAGE FORMS AND STRENGTHS

Topical gel: 1.2% clindamycin phosphate, 0.15% adapalene, and 3.1% benzoyl peroxide as a white to off-white, opaque gel.

CABTREO is supplied in 20-gram and 50-gram pumps.

4 CONTRAINDICATIONS

CABTREO is contraindicated in patients with:

- Known hypersensitivity to clindamycin, adapalene, benzoyl peroxide, any other components of CABTREO, or lincomycin [ see Warnings and Precautions(5.1)].
- A history of regional enteritis, ulcerative colitis, or antibiotic-associated colitis [ see Warnings and Precautions (5.2)].

5 WARNINGS AND PRECAUTIONS

5.1 Hypersensitivity

Hypersensitivity reactions, including anaphylaxis, angioedema, and urticaria, have been reported with use of clindamycin phosphate, benzoyl peroxide, and adapalene [see Adverse Reactions (6.2)]. If a serious hypersensitivity reaction occurs, discontinue CABTREO immediately and initiate appropriate therapy.

5.2 Colitis

Diarrhea, bloody diarrhea, and colitis have been reported with the use of topical and systemic clindamycin. Severe colitis has occurred with an onset of up to several weeks following cessation of therapy. Antiperistaltic agents such as opiates and diphenoxylate with atropine may prolong and/or worsen severe colitis. Severe colitis may result in death. Discontinue CABTREO if diarrhea occurs.

5.3 Photosensitivity

CABTREO may increase sensitivity to ultraviolet light. Avoid or minimize sun exposure (including use of tanning beds, and sun lamps) following CABTREO application. Instruct patients to use sunscreen products and wear protective apparel (e.g., hat) when exposure to sun cannot be avoided.

5.4 Skin Irritation and Allergic Contact Dermatitis

Stinging/burning/pain, erythema, dryness, irritation, exfoliation, and dermatitis have been reported with use of CABTREO. These application site adverse reactions occurred at a greater frequency in CABTREO-treated subjects than in vehicle-treated subjects. These adverse reactions are most likely to occur during the first four weeks of treatment [ see Adverse Reactions (6.1)] .

Irritant and allergic contact dermatitis have been reported with use of CABTREO.

Weather extremes, such as wind or cold, may be irritating to patients under treatment with CABTREO.

Depending upon the severity of these adverse reactions, instruct patients to use a moisturizer, reduce the frequency of the application of CABTREO, or discontinue use. Avoid applying CABTREO to areas of broken, eczematous, or sunburned skin. Avoid use of “waxing” as a depilatory method on skin treated with CABTREO.

Avoid concomitant use of other potentially irritating topical products such as peeling, desquamating, or abrasive agents and products with high concentrations of alcohol, astringents, spices, or limes.

Use of CABTREO with concomitant topical acne therapy has not been evaluated.

6 ADVERSE REACTIONS

The following adverse reactions are discussed in more detail in other sections of the labeling:

- Hypersensitivity [ see Warnings and Precautions (5.1)]
- Colitis [see Warnings and Precautions (5.2)]
- Skin Irritation and Allergic Contact Dermatitis [see Warnings and Precautions (5.4)]

6.1 Clinical Trials Experience

Because clinical trials are conducted under widely varying conditions, adverse reaction rates observed in the clinical trials of a drug cannot be directly compared to rates in the clinical trials of another drug and may not reflect the rates observed in clinical practice.

In two multicenter, randomized, double-blind, vehicle-controlled clinical trials (Trial 1 and Trial 2), 363 adult and pediatric subjects 10 years of age and older with facial acne vulgaris were treated with CABTREO or vehicle topically once daily for 12 weeks [see Clinical Studies (14)] . Adverse reactions reported by >1% of subjects treated with CABTREO and more frequently than subjects treated with vehicle are summarized in Table 1. These adverse reactions were mild (59%), moderate (36.4%), and severe (4.5%). Overall, 2.5% (6/242) of subjects discontinued CABTREO because of local skin reactions.

Table 1: Adverse Reactions Reported by >1% of Subjects with Facial Acne Vulgaris Treated with CABTREO (and More Frequently than Vehicle) in Trials 1 and 2
Adverse Reactions
N (%)
 | CABTREO N=242 | Vehicle N=121
Application site pain [Application site pain also includes application site stinging and burning] | 33 (13.6) | 1 (0.8)
Application site erythema [Application site erythema also includes erythema] | 11 (4.5) | 0
Application site dryness [Application site dryness also includes xerosis] | 10 (4.1) | 1 (0.8)
Application site irritation | 5 (2.1) | 0
Application site exfoliation | 4 (1.7) | 0
Application site dermatitis | 3 (1.2) | 0

Local tolerability evaluations were conducted at each study visit by assessment of erythema, scaling, itching, burning, and stinging. Table 2 presents the signs and symptoms of local facial tolerability during the 12 Week treatment period in subjects treated with CABTREO.

Table 2: Facial Cutaneous Tolerability Assessment During 12-Week Treatment Period in Subjects with Acne Vulgaris Treated with CABTREO in Trials 1 and 2
 | Maximum During Treatment [The denominators for calculating the percentages were the number of subjects with at least one post-baseline cutaneous tolerability assessment.] |  |  | Week 12 (End of Treatment) [The denominators for calculating the percentages were the number of subjects with Week 12 assessment.]
 | Mild (%) | Mod (%) | Severe (%) | Mild (%) | Mod (%) | Severe (%)
CABTREO (N = 242)
Erythema | 34.2 | 19.7 | 2.1 | 22.4 | 6.5 | 0.5
Burning | 29.6 | 10.7 | 3.0 | 4.2 | 1.4 | 0.9
Scaling | 26.7 | 3.4 | 0 | 7.0 | 0.9 | 0
Itching | 24.3 | 3.4 | 0.4 | 6.0 | 0.9 | 0
Stinging | 20.5 | 5.1 | 2.6 | 2.3 | 0.9 | 0.5
Vehicle (N = 121)
Erythema | 22.5 | 21.7 | 1.7 | 25.5 | 5.5 | 0
Burning | 2.5 | 0.8 | 0.8 | 0.9 | 0 | 0
Scaling | 12.5 | 0 | 0 | 4.5 | 0 | 0
Itching | 11.6 | 0.8 | 0 | 1.8 | 0 | 0
Stinging | 3.3 | 0.8 | 0 | 1.8 | 0 | 0

Local tolerability scores for erythema, scaling, itching, burning, and stinging increased during the first two weeks of treatment and decreased thereafter.

6.2 Postmarketing Experience

The following adverse reactions have been identified during post-approval use of products containing clindamycin phosphate, adapalene, and benzoyl peroxide as the active ingredients. Because post-marketing adverse reactions are reported voluntarily from a population of uncertain size, it is not always possible to reliably estimate their frequency or establish a causal relationship to drug exposure.

Immune system disorders:anaphylaxis and allergic reactions including eyelid edema, throat tightness, swelling of the face, and eczema. [see Contraindications (4)] .

Local Adverse Reactions:sunburn, blister, pruritis, hyperpigmentation and hypopigmentation.

Gastrointestinal Disorders:abdominal pain and gastrointestinal disturbances.

Bacterial infections:gram negative folliculitis

7 DRUG INTERACTIONS

Neuromuscular Blocking Agents

Clindamycin has been shown to have neuromuscular blocking properties that may enhance the action of other neuromuscular blocking agents. Use CABTREO with caution in patients receiving such agents.

8 USE IN SPECIFIC POPULATIONS

8.1 Pregnancy

Risk Summary

Available data with CABTREO use in pregnant women are insufficient to evaluate a drug-associated risk of major birth defects, miscarriage, or adverse maternal or fetal outcomes. Animal reproduction studies have not been conducted with CABTREO.

Clindamycin

In published clinical trials and observational studies with pregnant women, oral or IV administration of clindamycin has not been associated with an increased frequency of major birth defects, miscarriage, or other adverse maternal or fetal outcomes. In animal reproduction studies, clindamycin phosphate did not cause malformations or embryofetal development toxicity in pregnant rats and mice when administered during the period of organogenesis at systemic doses up to 192 times the maximum recommended human dose (MRHD) of 2.5 g CABTREO, based on a body surface area (mg/m^2) comparison.

Adapalene

Available data from clinical trials with adapalene topical gel use in pregnant women are insufficient to establish a drug-associated risk of major birth defects, miscarriage or other adverse maternal or fetal outcomes. In animal reproduction studies, oral administration of adapalene to pregnant rats and rabbits during organogenesis at doses 64 and 128 times, respectively, the MRHD resulted in fetal skeletal and visceral malformations (see Data).

Benzoyl peroxide

The systemic exposure of topical benzoyl peroxide is unknown. Based on published literature, benzoyl peroxide is rapidly metabolized to benzoic acid (an endogenous substance), which is eliminated in the urine. Hence, maternal use is not expected to result in fetal exposure of the drug.

The background risk of major birth defects and miscarriage for the indicated population is unknown. All pregnancies have a background risk of birth defect, loss, and other adverse outcomes. In the U.S. general population, the estimated background risk of major birth defects and miscarriage in clinically recognized pregnancies is 2 to 4% and 15 to 20%, respectively.

Data

Animal Data

Animal reproductive/developmental toxicity studies have not been conducted with CABTREO. Clindamycin phosphate administration during the period of organogenesis in pregnant rats and mice at oral doses up to 600 mg/kg/day (192 and 96 times the MRHD, respectively, based on a mg/m^2comparison) or subcutaneous doses up to 200 mg/kg/day (64 and 32 times the MRHD, respectively, based on a mg/m^2comparison) did not cause fetal malformations or fetotoxicity.

No malformations were observed in rats treated with oral adapalene doses of 0.15 to 5.0 mg/kg/day (up to 13 times the MRHD based on a mg/m^2comparison). However, malformations were observed in rats and rabbits when treated with oral doses of ≥ 25 mg/kg/day adapalene (64 and 128 times the MRHD, respectively, based on a mg/m^2comparison). Findings included cleft palate, microphthalmia, encephalocele, and skeletal abnormalities in rats and umbilical hernia, exophthalmos, and kidney and skeletal abnormalities in rabbits.

Dermal adapalene embryofetal development studies in rats and rabbits at doses up to 6.0 mg/kg/day adapalene (up to 15 and 30 times the MRHD, respectively, based on a mg/m^2comparison) exhibited no fetotoxicity and only minimal increases in skeletal variations (supernumerary ribs in both species and delayed ossification in rabbits).

8.2 Lactation

Risk Summary

The developmental and health benefits of breastfeeding should be considered along with the mother's clinical need for CABTREO and any potential adverse effects on the breastfed child from CABTREO or from the underlying maternal condition.

Clindamycin

There are no data on the presence of clindamycin in human milk, the effects on the breastfed child, or the effects on milk production following topical administration. However, clindamycin has been reported to be present in human milk in small amounts following oral and parenteral administration.

Adapalene

There are no data on the presence of topical adapalene gel or its metabolite in human milk, the effects on the breastfed infant, or the effects on milk production. In animal studies, adapalene is present in rat milk with oral administration of the drug. When a drug is present in animal milk, it is likely that the drug will be present in human milk. It is possible that topical administration of large amounts of adapalene could result in sufficient systemic absorption to produce detectable quantities in human milk (see Clinical Considerations).

Benzoyl peroxide

There are no data on the presence of topical benzoyl peroxide in human milk, its effects on the breastfed infant, or its effects on milk production. The systemic exposure of benzoyl peroxide is unknown. Based on the published literature, benzoyl peroxide is rapidly metabolized to benzoic acid (an endogenous substance), which is eliminated in the urine. Any amount of benzoyl peroxide excreted into human milk by a nursing mother would be expected to be rapidly metabolized by tissue and stomach esterases.

Clinical Considerations

To minimize potential exposure to the breastfed infant via breastmilk, use CABTREO on the smallest area of skin and for the shortest duration possible while breastfeeding. To avoid direct infant exposure, advise patients who are breastfeeding not to apply CABTREO directly to the nipple and areola. If applied to the patient’s chest, care should be taken to avoid infant exposure via direct contact with the infant skin.

8.4 Pediatric Use

The safety and effectiveness of CABTREO for the topical treatment of acne vulgaris have been established in pediatric patients 12 years of age and older. Use of CABTREO for this indication is supported by data from two randomized, double-blind, vehicle-controlled trials [ see Clinical Studies (14)].

The safety and effectiveness of CABTREO have not been established in pediatric patients younger than 12 years of age.

8.5 Geriatric Use

Clinical studies of CABTREO did not include any subjects 65 years of age and older to determine whether they respond differently from younger adult subjects.

11 DESCRIPTION

CABTREO (clindamycin phosphate, adapalene, and benzoyl peroxide) topical gel is a white to off-white, opaque gel. Each gram of CABTREO contains 12 mg (1.2%) clindamycin phosphate, equivalent to 10 mg (1%) clindamycin and 1.5 mg (0.15%) adapalene, and 31 mg (3.1%) benzoyl peroxide. Clindamycin phosphate is a water-soluble ester of the semisynthetic antibiotic produced by a 7(S)-chloro-substitution of the 7(R)-hydroxyl group of the parent antibiotic lincomycin. Adapalene, a synthetic retinoid, is a naphthoic acid derivative with retinoid-like properties. Benzoyl peroxide is an oxidizing agent.

The chemical name for clindamycin phosphate is Methyl-7-chloro-6,7,8-trideoxy-6-(1-methyl-trans-4-propyl-L-2-pyrrolidinecarboxamido)-1-thio-L-threo-α-D-galacto-octopyranoside 2-(dihydrogen phosphate). The structural formula for clindamycin phosphate is represented below:

Clindamycin phosphate:

Molecular Formula: C18H34ClN2O8PS
Molecular Weight: 504.97

The chemical name for adapalene is 6-[3-(1-Adamantyl)-4-methoxyphenyl]-2-naphthoic acid. The structural formula for adapalene is represented below:

Adapalene:

Molecular Formula: C28H28O3

Molecular Weight: 412.52

The chemical name for benzoyl peroxide is dibenzoyl peroxide. The structural formula for benzoyl peroxide is represented below:

Benzoyl peroxide:

Molecular Formula: C14H10O4
Molecular Weight: 242.23

CABTREO contains the following inactive ingredients: carbomer homopolymer type C (carbomer 980), potassium hydroxide, propylene glycol, and purified water.

12 CLINICAL PHARMACOLOGY

12.1 Mechanism of Action

Clindamycin:Clindamycin is a lincosamide antibacterial [see Microbiology (12.4)] .

Adapalene:Adapalene binds to specific retinoic acid nuclear receptors but does not bind to cytosolic receptor protein. Biochemical and pharmacological profile studies have demonstrated that adapalene is a modulator of cellular differentiation, keratinization and inflammatory processes. However, the significance of these findings with regard to the mechanism of action of adapalene for the treatment of acne is unknown.

Benzoyl Peroxide:Benzoyl peroxide is an oxidizing agent with bactericidal and keratolytic effects but the precise mechanism of action is unknown.

12.2 Pharmacodynamics

Pharmacodynamics of CABTREO are unknown.

12.3 Pharmacokinetics

Systemic exposure following topical application of CABTREO was evaluated in 28 subjects in an open-label, randomized, pharmacokinetic study. Subjects aged 12 years and older with moderate to severe acne vulgaris applied 2.2 ± 0.4 (mean ± SD) grams of CABTREO to the entire face (excluding eyes and lips), neck, upper chest, upper back and shoulders once daily for 28 days.

Clindamycin phosphate concentrations were measurable in the majority of samples following single and repeated topical administration of CABTREO (LOQ = 0.05 ng/mL). The mean Cmaxand mean AUC[0-t]values for clindamycin phosphate were 2.44 ng/mL (range: 0.15 to 6.14 ng/mL) and 30.7 ng•h/mL (range: 1.04 to 87.4 ng•h/mL) on Days 28-29, respectively. Clindamycin (Cmaxand AUC[0-t]) accumulated up to approximately 3-fold between Days 1-2 and Days 28-29 following once daily application of CABTREO.

Adapalene concentrations were measurable in the majority of samples following single and repeated topical administration of CABTREO (LOQ = 0.10 ng/mL). The mean Cmaxand mean AUC(0-t)values for adapalene were 0.10 ng/mL (range: 0 to 0.27 ng/mL) and 2.40 ng•h/mL (range: 0.56 to 3.87 ng•h/mL) on Days 28-29, respectively. Adapalene (AUC[0-t]) accumulated up to approximately 3-fold between Days 1-2 and Days 28-29 for CABTREO.

Benzoyl peroxide is absorbed by the skin where it is converted to benzoic acid and eliminated in the urine.

Drug Interaction Studies

In Vitro Studies

Erythromycin products:Concurrent use with erythromycin topical or oral products may reduce the efficacy of CABTREO. This finding is based upon the mechanistic understanding of these drugs and published in vitro antagonism between erythromycin and clindamycin. This finding was not confirmed by a dedicated clinical study. While the clinical significance of this finding is unknown, it still warrants consideration given the potential impact on the efficacy of CABTREO.

12.4 Microbiology

Clindamycin binds to the 50S ribosomal subunits of susceptible bacteria and prevents elongation of peptide chains by interfering with peptidyl transfer, thereby suppressing bacterial protein synthesis.

Clindamycin and benzoyl peroxide individually have been shown to have in vitro activity against Cutibacterium acnes (C. acnes), an organism which has been associated with acne vulgaris. In an in vitro study, the minimum inhibitory concentration (MIC) for benzoyl peroxide against C. acnesis 128 mg/L. The clinical significance of this activity against C. acnesis not known.

C. acnesresistance to clindamycin has been documented. Resistance to clindamycin is often associated with resistance to erythromycin.

13 NONCLINICAL TOXICOLOGY

13.1 Carcinogenesis, Mutagenesis, Impairment of Fertility

No carcinogenicity, genotoxicity, or fertility studies were conducted with CABTREO.

Carcinogenicity studies have been conducted with a gel formulation containing 1% clindamycin phosphate and 5% benzoyl peroxide. In a 2-year dermal carcinogenicity study in mice, treatment with the gel formulation at doses up to 15,000 mg/kg/day (up to 24 times the MRHD for clindamycin phosphate and up to 47 times the MRHD for benzoyl peroxide based on a mg/m^2comparison) did not cause any increase in tumors. However, in a 2-year dermal carcinogenicity study in rats using a different gel formulation containing 1% clindamycin phosphate and 5% benzoyl peroxide increased the incidence of keratoacanthoma at the treated skin site of male rats treated with 2,000 mg/kg/day (6.4 times the MRHD for clindamycin phosphate and 12.4 times the MRHD for benzoyl peroxide based on a mg/m^2comparison). In an oral (gavage) carcinogenicity study in rats, treatment with the gel formulation at doses up to 3,000 mg/kg/day (up to 10 times the MRHD for clindamycin phosphate and up to 19 times the MRHD for benzoyl peroxide based on a mg/m^2comparison) for up to 97 weeks did not cause any increase in tumors.

Carcinogenicity studies with adapalene were conducted in mice at topical doses of 0.4, 1.3, and 4.0 mg/kg/day of adapalene, and in rats at oral doses of 0.15, 0.5, and 1.5 mg/kg/day of adapalene. The highest dose levels are 5.1 (mice) and 3.8 (rats) times the MRHD based on a mg/m^2comparison. In the rat study, an increased incidence of benign and malignant pheochromocytomas reported in the adrenal medulla of male rats was observed.

Benzoyl peroxide is a tumor promoter in several animal species. The significance of this finding in humans is unknown.

Clindamycin phosphate was not genotoxic in the human lymphocyte chromosome aberration assay.

Bacterial mutagenicity assays (Ames test) with benzoyl peroxide provided mixed results; mutagenic potential was observed in a few but not in a majority of investigations. It has been shown to produce single-strand DNA breaks in human bronchial epithelial and mouse epidermal cells, caused DNA-protein cross-links in the human cells, and also induced a dose-dependent increase in sister chromatid exchanges in Chinese hamster ovary cells.

Adapalene did not exhibit mutagenic or genotoxic effects in vitro (Ames test, Chinese hamster ovary cell assay, or mouse lymphoma TK assay) or in vivo (mouse micronucleus test).

Fertility studies in rats treated orally with up to 300 mg/kg/day of clindamycin phosphate (approximately 96 times the MRHD based on a mg/m^2comparison) revealed no effects on fertility or mating ability.

In rat oral studies, 20 mg/kg/day adapalene (51 times the MRHD based on a mg/m^2comparison) did not affect the reproductive performance and fertility of F0males and females, or the growth, development and reproductive function of F1offspring.

14 CLINICAL STUDIES

The efficacy of CABTREO was evaluated in two multicenter, randomized, double-blind clinical trials (Trial 1 and Trial 2, NCT04214639 and 2 NCT04214652, respectively) in 363 adult and pediatric subjects 10 years of age and older with facial acne vulgaris. While subjects aged 10 to less than 12 years were included in these trials, CABTREO is not approved for use in patients less than 12 years of age.

Subjects were randomized 2:1 to receive CABTREO or vehicle applied once daily for 12 weeks. The trial population included 74% White, 15% Black or African American, 7% Asian, 4% Other, and <1% Native Hawaiian or Other Pacific Islander; for ethnicity, 78% identified as non-Hispanic/Latino and 22% identified as Hispanic/Latino. Fifty-eight percent were female and 42% were male. The median age of the trial population was 18 years (range: 10 to 48 years). Enrolled subjects had a score of moderate (3) or severe (4) on the Evaluator’s Global Severity Score (EGSS), 30 to 100 inflammatory lesions (papules, pustules, and nodules), 35 to 150 non-inflammatory lesions (open and closed comedones) and two or fewer facial nodules. At baseline, most subjects (91%) had EGSS scores that equated to moderate acne. The co-primary efficacy endpoints of success on the EGSS, absolute change in noninflammatory lesion count, and absolute change in inflammatory lesion count were assessed at Week 12. Success on the EGSS was defined as at least a 2-grade improvement from baseline and an EGSS score of clear (0) or almost clear (1).

Table 3 lists the efficacy results for Trials 1 and 2.

Table 3: Efficacy Results at Week 12

Table 3: Efficacy Results at Week 12 in Subjects with Facial Acne Vulgaris in Trials 1 and 2
Trial 1 | CABTREO N=122 | Vehicle N=61 | Treatment Difference (95% Confidence Interval)
EGSS
Clear or Almost Clear and 2-Grade Reduction from Baseline | 49.6% | 24.9% | 24.7 (10.7, 38.7)
Non-Inflammatory Facial Lesions
Mean Absolute Reduction | 35.4 | 23.5 | 11.9 (7.1, 16.6)
Mean Percent Reduction | 72.7% | 47.6%
Inflammatory Facial Lesions
Mean Absolute Reduction | 27.7 | 21.7 | 5.9 (3.1, 8.7)
Mean Percent Reduction | 75.7% | 59.6%
Trial 2 | CABTREO N=120 | Vehicle N=60
EGSS
Clear or Almost Clear and; 2-Grade Reduction from Baseline | 50.5% | 20.5% | 30.0 (16.4, 43.6)
Non-Inflammatory Facial Lesions
Mean Absolute Reduction | 35.2 | 22.0 | 13.3 (8.8, 17.7)
Mean Percent Reduction | 73.3% | 49.0%
Inflammatory Facial Lesions
Mean Absolute Reduction | 30.1 | 20.8 | 9.3 (6.2, 12.4)
Mean Percent Reduction | 80.1% | 56.2%

16 HOW SUPPLIED/STORAGE AND HANDLING

How Supplied

CABTREO (clindamycin phosphate, adapalene, and benzoyl peroxide) topical gel is a white to off-white, opaque topical gel. CABTREO contains 1.2% clindamycin phosphate, 0.15% adapalene, and 3.1% benzoyl peroxide and is supplied as follows:

- 20 g pump (NDC 0187-0006-10)
- 50 g pump (NDC 0187-0006-25)

Storage and Handling

- Prior to Dispensing:Store CABTREO in a refrigerator between 2° to 8°C (36° to 46°F) until dispensed to the patient. Dispense CABTREO with a 10-week expiration date.
- After Dispensing:Store CABTREO at room temperature at or below 25°C (77°F).
- Do not freeze.
- Keep away from heat.
- Store pump upright.

17 PATIENT COUNSELING INFORMATION

Advise the patient to read the FDA-approved patient labeling (Patient Information).

Administration Instructions

Advise patients to apply CABTREO as a thin layer to affected areas, avoiding the eyes, lips, paranasal creases, mucous membranes, and areas of broken, eczematous, or sunburned skin [see Dosage and Administration (2)] .

Instruct patients to wash hands after application. [see Dosage and Administration (2)] .

Advise patients that CABTREO may bleach hair and colored fabric.

Hypersensitivity

Inform patients that hypersensitivity reactions may occur. Advise patients to discontinue use of CABTREO and contact their healthcare provider immediately if symptoms of an allergic reaction, such as severe swelling or shortness of breath, occur [see Warnings and Precautions (5.1), Contraindications (4)] .

Colitis

Advise patients to discontinue use of CABTREO and contact their healthcare provider if diarrhea occurs [ see Warnings and Precautions (5.2)] .

Photosensitivity

Advise patients to minimize or avoid exposure to sunlight or sunlamps, including tanning beds. Instruct patients to use sunscreen and wear protective clothing (e.g., hat) over treated areas when exposure to sun cannot be avoided [see Warnings and Precautions (5.3)] .

Skin Irritation and Allergic Contact Dermatitis

Inform patients that CABTREO may cause irritation, such as erythema, scaling, dryness, itching, stinging or burning. Depending on the severity of the reactions, advise patients to use a moisturizer, reduce the frequency of application, or discontinue use of CABTREO [see Warnings and Precautions (5.4)] .

Lactation

Advise patients to use CABTREO on the smallest area of skin and for the shortest duration possible while breastfeeding. To avoid direct infant exposure, instruct patients who are breastfeeding not to apply CABTREO directly to the nipple and areola. Instruct patients to avoid inadvertent contact of treated areas with infant skin [ see Use in Specific Populations (8.2)].

Distributed by:
Bausch Health US, LLC
Bridgewater, NJ 08807 USA

Manufactured by:
Bausch Health Companies Inc.
Laval, Quebec H7L 4A8, Canada

Patented. See https://patents.ortho-dermatologics.com for US patent information.

CABTREO is a trademark of Bausch Health Companies Inc. or its affiliates.

© 2025 Bausch Health Companies Inc. or its affiliates
90001201

Patient Package Insert

PATIENT INFORMATION
CABTREO®(kab-TREE-oh)
(clindamycin phosphate, adapalene and benzoyl peroxide)
topical gel

Important information:CABTREO is for use on skin only (topical use). Do not use CABTREO in your mouth, eyes, or vagina.

What is CABTREO?

CABTREO is a prescription medicine used on the skin (topical) to treat acne vulgaris in adults and children 12 years of age and older.

It is not known if CABTREO is safe and effective in children under 12 years of age.

Do not use CABTREO if you have:

- had an allergic reaction to clindamycin, adapalene, benzoyl peroxide, lincomycin, or any of the ingredients in CABTREO. See the end of this Patient Information leaflet for a complete list of ingredients in CABTREO.
- Crohn's disease or ulcerative colitis.
- had inflammation of the colon (colitis), or severe diarrhea with past antibiotic use.

Talk with your healthcare provider if you are not sure if you have any of the conditions listed above.

Before using CABTREO, tell your healthcare provider about all of your medical conditions, including if you:

- plan to have surgery. CABTREO may affect how certain medicines work that may be given during surgery.
- are pregnant or plan to become pregnant. It is not known if CABTREO will harm your unborn baby.
- are breastfeeding or plan to breastfeed. It is not known if CABTREO passes into your breast milk. Clindamycin when taken by mouth or by injection has been reported to appear in breast milk. Talk to your healthcare provider about the best way to feed your baby during treatment with CABTREO.
- If you use CABTREO while breastfeeding:
- use CABTREO on the smallest area of skin and for the shortest time needed.
- do notapply CABTREO directly to the nipple and areola to avoid getting CABTREO into your baby’s mouth.
- avoid direct skin contact with your baby if CABTREO is applied to your chest.

Tell your healthcare provider about all the medicines you take,including prescription and over-the-counter medicines, vitamins, and herbal supplements.

- Especially tell your healthcare providerif you take medicine by mouth that contains erythromycin or use products on your skin that contain erythromycin. CABTREO should not be used with products that contain erythromycin.
  Especially tell your healthcare provider about any skin products you use. Other skin and topical acne products may increase the irritation of your skin when used with CABTREO.

Know the medicines you take. Keep a list of them to show to your healthcare provider and pharmacist when you get a new medicine.

How should I use CABTREO?

- Use CABTREO exactly as your healthcare provider tells you to use it. See the detailed “Instructions for Use”for directions about how to apply CABTREO.
- Apply a thin layer of CABTREO to cover the treatment area 1 time each day.
- Avoid applying CABTREO to the eyes, lips, creases around your nose, your mouth, and areas of your skin with cuts, abrasions, or sunburned skin.
- Before you apply CABTREO, wash your face gently with a mild or soapless cleanser, rinse with warm water, and pat your skin dry.
- Wash your hands right away after applying CABTREO.

1. What should I avoid during treatment with CABTREO?
2. Avoid or limit your time in sunlight, including use of tanning beds or sunlamps during treatment with CABTREO. CABTREO can make you more sensitive to the sun, and the light from sunlamps and tanning beds. You could get severe sunburn. Use sunscreen and wear wide-brimmed hat and clothes that cover the treated area of your skin if you have to be in sunlight.
3. Cold weather and wind may irritate skin treated with CABTREO.
4. Avoid applying CABTREO to areas with skin problems, including cuts, abrasions, sunburn, or eczema.
5. Avoid skin products that may dry or irritate your skin such as medicated or harsh soaps, astringents, cosmetics that make your skin dry, and products containing high levels of alcohol, spices, or limes.
6. Avoid the use of “waxing” as a hair removal method on skin treated with CABTREO.
7. Avoid getting CABTREO in your hair or on colored fabric. CABTREO may bleach hair or colored fabric.

What are the possible side effects of CABTREO?

CABTREO may cause serious side effects, including:

- Allergic reactions.Stop using CABTREO, and get help right away if you have any of the following symptoms during treatment with CABTREO:
  - hives, rash, or severe itching
  - swelling of your face, eyes, lips, tongue, or throat
  - trouble breathing or throat tightness
  - feeling faint, dizzy, or lightheaded
- Inflammation of the colon (colitis).Stop using CABTREO and call your healthcare provider right away if you have severe stomach (abdominal) cramps, watery diarrhea, or bloody diarrhea during treatment, and within several weeks after treatment with CABTREO.
- Sensitivity to sunlight.See “What should I avoid while using CABTREO?”
- Skin irritation.Skin irritation is common with CABTREO and is most likely to happen during the first 4 weeks of treatment, and usually lessen with continued use of CABTREO. Skin reactions at the treatment area include redness, scaling, dryness, stinging, burning, itching, and swelling. Tell your healthcare provider if you get any skin reactions.

Tell your healthcare provider if you have any side effect that bothers you or that does not go away.

These are not all of the possible side effects of CABTREO.

Call your doctor for medical advice about side effects. You may report side effects to FDA at 1-800-FDA-1088.

How should I store CABTREO?

- Store CABTREO at room temperature at or below 77°F (25°C).
- Do not freeze CABTREO.
- Keep CABTREO away from heat.
- Store CABTREO pump upright.
- Throw away (discard) CABTREO that has passed the expiration date.

Keep CABTREO and all medicines out of the reach of children.

General information about the safe and effective use of CABTREO.

Medicines are sometimes prescribed for purposes other than those listed in a Patient Information leaflet. Do not use CABTREO for a condition for which it was not prescribed. Do not give CABTREO to other people, even if they have the same symptoms that you have. It may harm them. You can ask your pharmacist or healthcare provider for information about CABTREO that is written for health professionals.

What are the ingredients in CABTREO?

Active ingredient:clindamycin phosphate, adapalene, and benzoyl peroxide.

Inactive ingredients:carbomer homopolymer type C (carbomer 980), potassium hydroxide, propylene glycol, and purified water.

Distributed by:Bausch Health US, LLC, Bridgewater, NJ 08807 USA

Manufactured by:Bausch Health Companies Inc., Laval, Quebec H7L 4A8, Canada

Patented. See https://patents.ortho-dermatologics.com for US patent information.

CABTREO is a trademark of Bausch Health Companies Inc. or its affiliates.

© 2025 Bausch Health Companies Inc. or its affiliates

For more information about CABTREO, call 1-800-321-4576.

- This Patient Information has been approved by the U.S. Food and Drug Administration.
- Revised: 03/2025
- 90001201

Instructions for Use

CABTREO®(kab-TREE-oh)
(clindamycin phosphate, adapalene and benzoyl peroxide)

topical gel

This Instructions for Use contains information on how to apply CABTREO.

Important information: CABTREO is for use on skin only (topical use). CABTREO is not for use in your mouth, eyes, or vagina.

Read this Instructions for Use before you start using CABTREO and each time you get a refill. There may be new information. This information does not take the place of talking with your healthcare provider about your medical condition or treatment.

- Apply CABTREO to your face 1 time each day as prescribed.
- Before you apply CABTREO, wash your face gently with a cleanser, rinse with warm water, and pat your skin dry.

Step 1

To apply CABTREO to your face, use the pump to dispense one pea-sized amount of CABTREO onto your fingertip. See Figure 1.

1. Note: One pea-sized amount of CABTREO should be enough to cover your entire face.

Figure 1

Step 2

Dot the one pea-sized amount of CABTREO onto six areas of your face (chin, left cheek, right cheek, nose, left forehead, right forehead). See Figure 2.

Figure 2

Step 3

Spread the gel over your face and gently rub it in. It is important to spread the gel over your entire face.If your healthcare provider tells you to put CABTREO on other areas of your skin with acne, be sure to ask how much you should use.

Step 4

Wash your hands after applying CABTREO.

How should I store CABTREO?

- Store CABTREO at room temperature at or below 77°F (25°C).
- Do not freeze CABTREO.
- Keep CABTREO away from heat.
- Store CABTREO pump upright.
- Throw away (discard) CABTREO that has passed the expiration date.

Keep CABTREO and all medicines out of the reach of children.

Distributed by:Bausch Health US, LLC, Bridgewater, NJ 08807 USA

Manufactured by:Bausch Health Companies Inc., Laval, Quebec H7L 4A8, Canada

Patented. See https://patents.ortho-dermatologics.com for US patent information.

CABTREO is a trademark of Bausch Health Companies Inc. or its affiliates.

© 2025 Bausch Health Companies Inc. or its affiliates

This Instructions for Use has been approved by the U.S. Food and Drug Administration. Revised: 03/2025

90001201

PACKAGE/LABEL PRINCIPAL DISPLAY PANEL

NDC0187-0006-25

Rx only

CABTREO®
(clindamycin phosphate, adapalene
and benzoyl peroxide) Topical Gel
1.2%/0.15%/3.1%

Not for Oral, Ophthalmic,
or Intravaginal Use

KEEP OUT OF
REACH OF
CHILDREN

Net Wt. 50 g

ORTHO Dermatologics

90000701